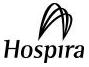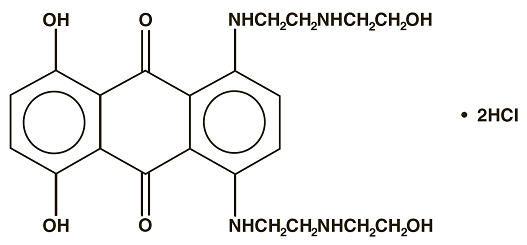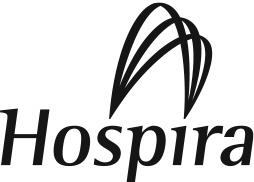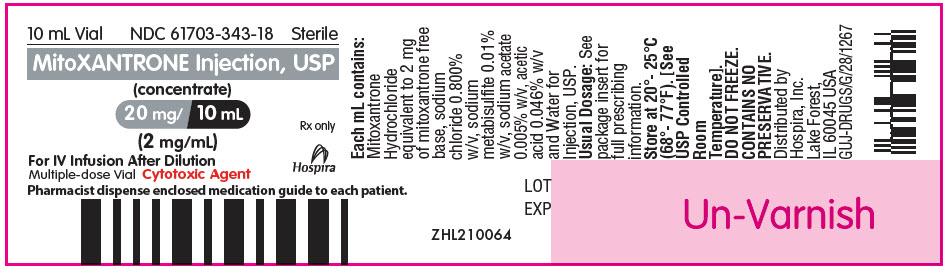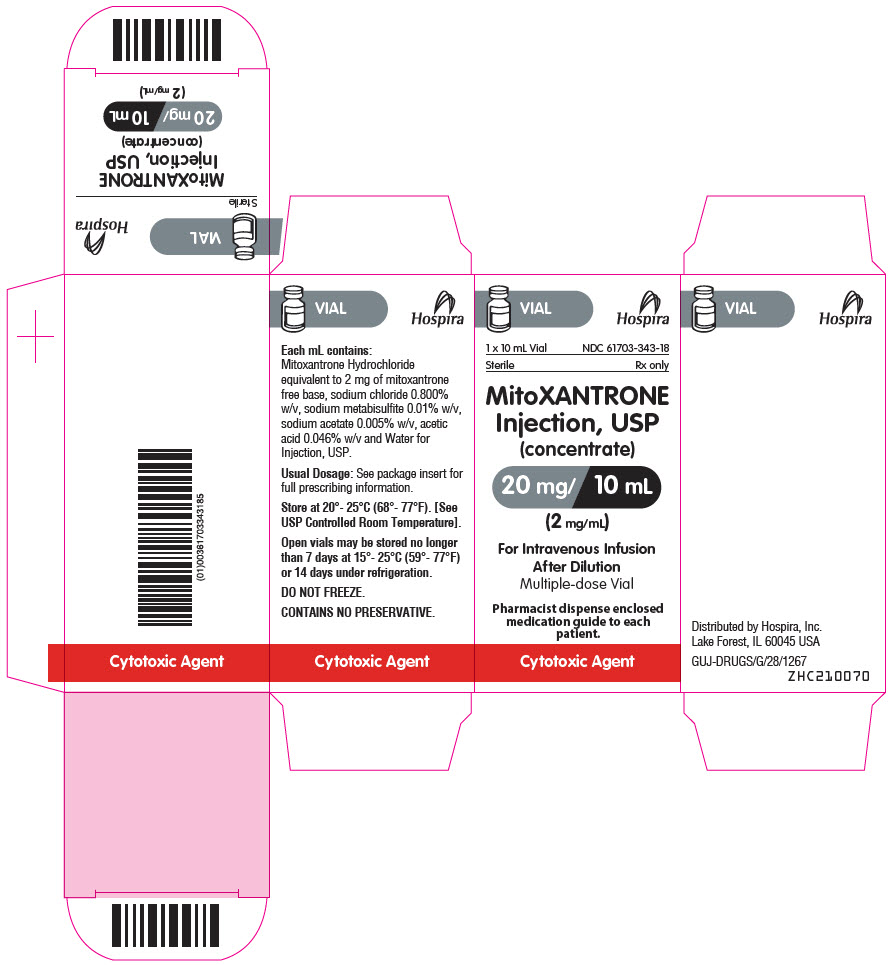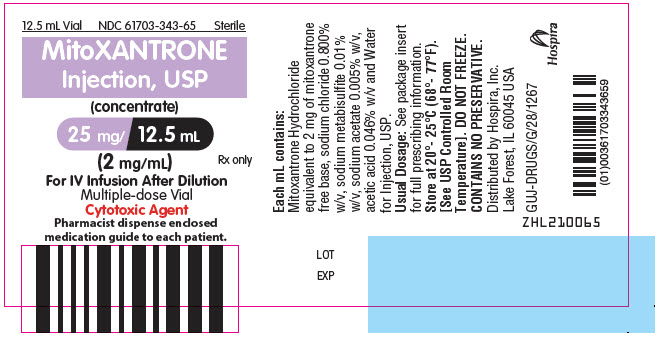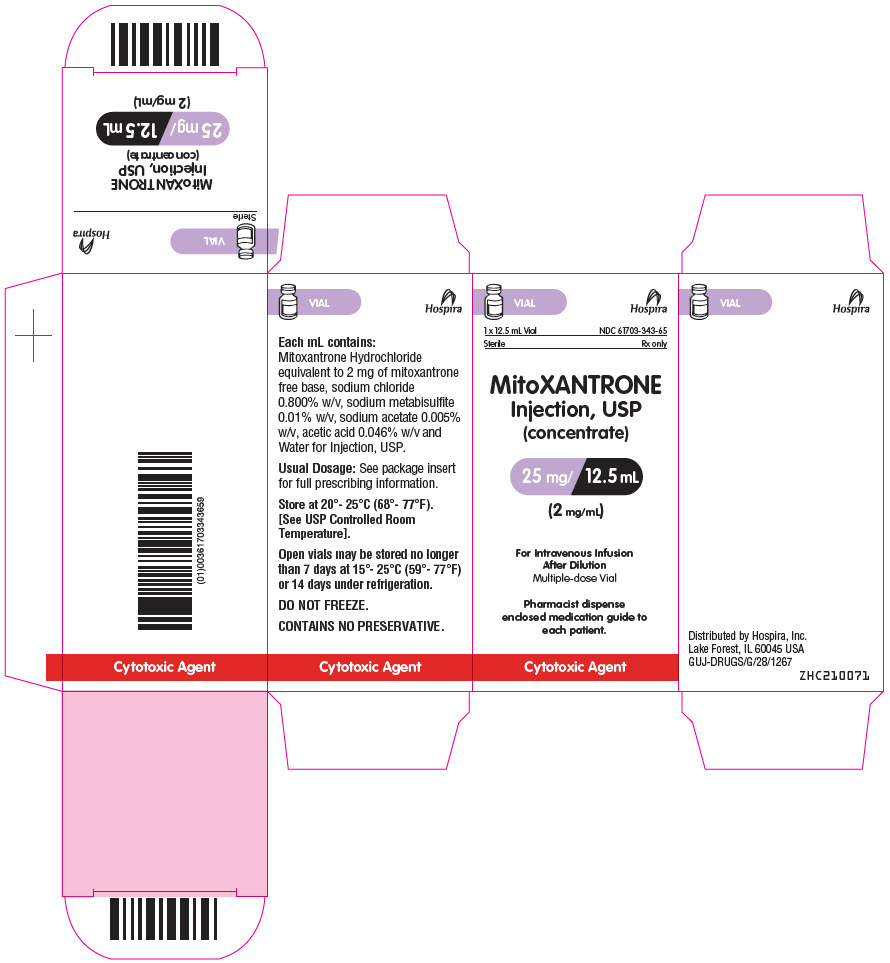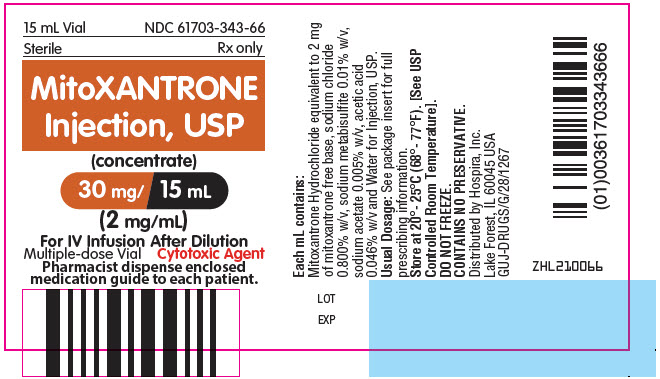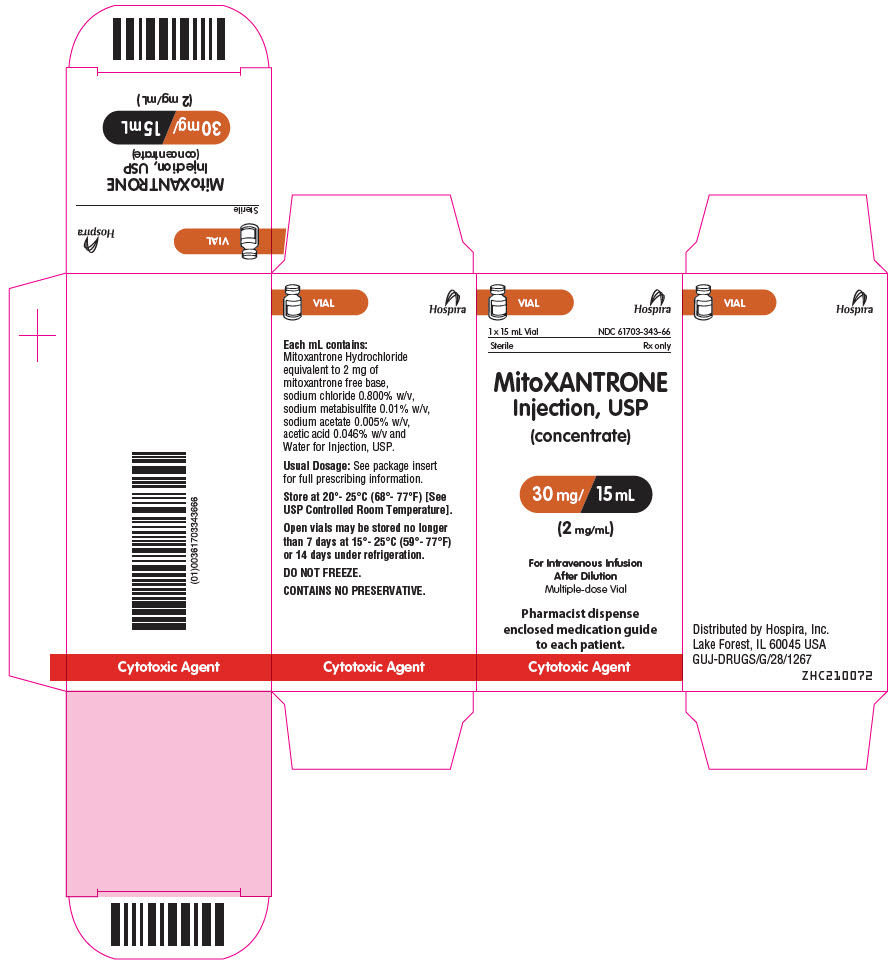 DRUG LABEL: Mitoxantrone
NDC: 61703-343 | Form: INJECTION, SOLUTION, CONCENTRATE
Manufacturer: Hospira, Inc.
Category: prescription | Type: HUMAN PRESCRIPTION DRUG LABEL
Date: 20250714

ACTIVE INGREDIENTS: MITOXANTRONE HYDROCHLORIDE 2 mg/1 mL
INACTIVE INGREDIENTS: SODIUM CHLORIDE; SODIUM ACETATE; ACETIC ACID; WATER; SODIUM METABISULFITE

MitoXANTRONE Injection, USP
(concentrate)

Rx only

WARNING

Mitoxantrone Injection, USP (concentrate) should be administered under the supervision of a physician experienced in the use of cytotoxic chemotherapy agents.

Mitoxantrone Injection, USP (concentrate) should be given slowly into a freely flowing intravenous infusion. It must never be given subcutaneously, intramuscularly, or intra-arterially. Severe local tissue damage may occur if there is extravasation during administration. (See ADVERSE REACTIONS, General, Cutaneous and DOSAGE AND ADMINISTRATION, Preparation and Administration Precautions).

NOT FOR INTRATHECAL USE. Severe injury with permanent sequelae can result from intrathecal administration. (See WARNINGS, General)

Except for the treatment of acute nonlymphocytic leukemia, mitoxantrone therapy generally should not be given to patients with baseline neutrophil counts of less than 1,500 cells/mm^3. In order to monitor the occurrence of bone marrow suppression, primarily neutropenia, which may be severe and result in infection, it is recommended that frequent peripheral blood cell counts be performed on all patients receiving mitoxantrone.

Cardiotoxicity:

Congestive heart failure (CHF), potentially fatal, may occur either during therapy with mitoxantrone or months to years after termination of therapy. Cardiotoxicity risk increases with cumulative mitoxantrone dose and may occur whether or not cardiac risk factors are present. Presence or history of cardiovascular disease, radiotherapy to the mediastinal/pericardial area, previous therapy with other anthracyclines or anthracenediones, or use of other cardiotoxic drugs may increase this risk. In cancer patients, the risk of symptomatic CHF was estimated to be 2.6% for patients receiving up to a cumulative dose of 140 mg/m^2. To mitigate the cardiotoxicity risk with mitoxantrone, prescribers should consider the following:

All Patients:

- All patients should be assessed for cardiac signs and symptoms by history, physical examination, and ECG prior to start of mitoxantrone therapy.
- All patients should have baseline quantitative evaluation of left ventricular ejection fraction (LVEF) using appropriate methodology (ex. Echocardiogram, multi-gated radionuclide angiography (MUGA), MRI, etc.).

Multiple Sclerosis Patients:

- MS patients with a baseline LVEF below the lower limit of normal should not be treated with mitoxantrone.
- MS patients should be assessed for cardiac signs and symptoms by history, physical examination and ECG prior to each dose.
- MS patients should undergo quantitative reevaluation of LVEF prior to each dose using the same methodology that was used to assess baseline LVEF. Additional doses of mitoxantrone should not be administered to multiple sclerosis patients who have experienced either a drop in LVEF to below the lower limit of normal or a clinically significant reduction in LVEF during mitoxantrone therapy.
- MS patients should not receive a cumulative mitoxantrone dose greater than 140 mg/m^2.
- MS patients should undergo yearly quantitative LVEF evaluation after stopping mitoxantrone to monitor for late occurring cardiotoxicity.

For additional information, see WARNINGS and DOSAGE AND ADMINISTRATION.

Secondary Leukemia:

Mitoxantrone therapy in patients with MS and in patients with cancer increases the risk of developing secondary acute myeloid leukemia.

DESCRIPTION

Mitoxantrone Injection, USP (concentrate) is a synthetic antineoplastic anthracenedione for intravenous use. The molecular formula is C22H28N4O6∙2HCl and the molecular weight is 517.41. It is supplied as a concentrate that MUST BE DILUTED PRIOR TO INJECTION. The concentrate is a sterile, nonpyrogenic, dark blue aqueous solution containing mitoxantrone hydrochloride equivalent to 2 mg/mL mitoxantrone free base, with sodium chloride (0.80% w/v), sodium metabisulfite (0.01% w/v), sodium acetate (0.005% w/v), acetic acid (0.046% w/v), and Water for Injection, USP as inactive ingredients. The solution has a pH of 3.0 to 4.5 and contains 0.14 mEq of sodium per mL. The product does not contain preservatives. The chemical name is 1, 4-dihydroxy-5, 8-bis[[2-[(2-hydroxyethyl) amino]ethyl]amino]-9,10- anthracenedione dihydrochloride and the structural formula is:

CLINICAL PHARMACOLOGY

Mechanism of Action

Mitoxantrone, a DNA-reactive agent that intercalates into deoxyribonucleic acid (DNA) through hydrogen bonding, causes crosslinks and strand breaks. Mitoxantrone also interferes with ribonucleic acid (RNA) and is a potent inhibitor of topoisomerase II, an enzyme responsible for uncoiling and repairing damaged DNA. It has a cytocidal effect on both proliferating and nonproliferating cultured human cells, suggesting lack of cell cycle phase specificity.

Mitoxantrone has been shown in vitro to inhibit B cell, T cell, and macrophage proliferation and impair antigen presentation, as well as the secretion of interferon gamma, TNFα, and IL-2.

Pharmacokinetics

Pharmacokinetics of mitoxantrone in patients following a single intravenous administration of mitoxantrone can be characterized by a three-compartment model. The mean alpha half-life of mitoxantrone is 6 to 12 minutes, the mean beta half-life is 1.1 to 3.1 hours and the mean gamma (terminal or elimination) half-life is 23 to 215 hours (median approximately 75 hours). Pharmacokinetic studies have not been performed in humans receiving multiple daily dosing. Distribution to tissues is extensive: steady-state volume of distribution exceeds 1,000 L/m^2. Tissue concentrations of mitoxantrone appear to exceed those in the blood during the terminal elimination phase. In the healthy monkey, distribution to brain, spinal cord, eye, and spinal fluid is low.

In patients administered 15 to 90 mg/m^2 of mitoxantrone intravenously, there is a linear relationship between dose and the area under the concentration-time curve (AUC).

Mitoxantrone is 78% bound to plasma proteins in the observed concentration range of 26 to 455 ng/mL. This binding is independent of concentration and is not affected by the presence of phenytoin, doxorubicin, methotrexate, prednisone, prednisolone, heparin, or aspirin.

Metabolism and Elimination

Mitoxantrone is excreted in urine and feces as either unchanged drug or as inactive metabolites. In human studies, 11% and 25% of the dose were recovered in urine and feces, respectively, as either parent drug or metabolite during the 5-day period following drug administration. Of the material recovered in urine, 65% was unchanged drug. The remaining 35% was composed of monocarboxylic and dicarboxylic acid derivatives and their glucuronide conjugates. The pathways leading to the metabolism of mitoxantrone have not been elucidated.

Special Populations

Gender

The effect of gender on mitoxantrone pharmacokinetics is unknown.

Geriatric

In elderly patients with breast cancer, the systemic mitoxantrone clearance was 21.3 L/hr/m^2, compared with 28.3 L/hr/m^2 and 16.2 L/hr/m^2 for non-elderly patients with nasopharyngeal carcinoma and malignant lymphoma, respectively.

Pediatric

Mitoxantrone pharmacokinetics in the pediatric population are unknown.

Race

The effect of race on mitoxantrone pharmacokinetics is unknown.

Renal Impairment

Mitoxantrone pharmacokinetics in patients with renal impairment are unknown.

Hepatic Impairment

Mitoxantrone clearance is reduced by hepatic impairment. Patients with severe hepatic dysfunction (bilirubin > 3.4 mg/dL) have an AUC more than three times greater than that of patients with normal hepatic function receiving the same dose. Patients with multiple sclerosis who have hepatic impairment should ordinarily not be treated with mitoxantrone. Other patients with hepatic impairment should be treated with caution and dosage adjustment may be required.

Drug Interactions

In vitro drug interaction studies have demonstrated that mitoxantrone did not inhibit CYP450 1A2, 2A6, 2C9, 2C19, 2D6, 2E1, and 3A4 across a broad concentration range. The results of in vitro induction studies are inconclusive, but suggest that mitoxantrone may be a weak inducer of CYP450 2E1 activity.

Pharmacokinetic studies of the interaction of mitoxantrone with concomitantly administered medications in humans have not been performed. The pathways leading to the metabolism of mitoxantrone have not been elucidated. To date, post-marketing experience has not revealed any significant drug interactions in patients who have received mitoxantrone for treatment of cancer. Information on drug interactions in patients with multiple sclerosis is limited.

CLINICAL TRIALS

Multiple Sclerosis

The safety and efficacy of mitoxantrone in multiple sclerosis were assessed in two randomized, multicenter clinical studies.

One randomized, controlled study (Study 1) was conducted in patients with secondary progressive or progressive relapsing multiple sclerosis. Patients in this study demonstrated significant neurological disability based on the Kurtzke Expanded Disability Status Scale (EDSS). The EDSS is an ordinal scale with 0.5 point increments ranging from 0.0 to 10.0 (increasing score indicates worsening) and based largely on ambulatory impairment in its middle range (EDSS 4.5 to 7.5 points). Patients in this study had experienced a mean deterioration in EDSS of about 1.6 points over the 18 months prior to enrollment.

Patients were randomized to receive placebo, 5 mg/m^2 mitoxantrone, or 12 mg/m^2 mitoxantrone administered IV every 3 months for 2 years. High-dose methylprednisolone was administered to treat relapses. The intent-to-treat analysis cohort consisted of 188 patients; 149 completed the 2-year study. Patients were evaluated every 3 months, and clinical outcome was determined after 24 months. In addition, a subset of patients was assessed with magnetic resonance imaging (MRI) at baseline, Month 12, and Month 24. Neurologic assessments and MRI reviews were performed by evaluators blinded to study drug and clinical outcome, although the diagnosis of relapse and the decision to treat relapses with steroids were made by unblinded treating physicians. A multivariate analysis of five clinical variables (EDSS, Ambulation Index [AI], number of relapses requiring treatment with steroids, months to first relapse needing treatment with steroids, and Standard Neurological Status [SNS]) was used to determine primary efficacy. The AI is an ordinal scale ranging from 0 to 9 in one point increments to define progressive ambulatory impairment. The SNS provides an overall measure of neurologic impairment and disability, with scores ranging from 0 (normal neurologic examination) to 99 (worst possible score).

Results of Study 1 are summarized in Table 1.

Table 1: Efficacy Results at Month 24 Study 1
 | Treatment Groups |  |  | p-value
 |  | Mitoxantrone |  | Placebo vs.
Primary Endpoints | Placebo (N = 64) | 5 mg/m^2 (N = 64) | 12 mg/m^2 (N = 60) | 12 mg/m^2 Mitoxantrone
Primary efficacy multivariate analysis [Wei-Lachin test.] | - | - | - | < 0.0001
Primary clinical variables analyzed:
EDSS change [Month 24 value minus baseline.] (mean) | 0.23 | – 0.23 | – 0.13 | 0.0194
Ambulation Index change (mean) | 0.77 | 0.41 | 0.30 | 0.0306
Mean number of relapses per patient requiring corticosteroid treatment (adjusted for discontinuation) | 1.20 | 0.73 | 0.40 | 0.0002
Months to first relapse requiring corticosteroid treatment (median [1st quartile]) | 14.2 [6.7] | NR [6.9] | NR [20.4] | 0.0004
Standard Neurological Status change (mean) | 0.77 | – 0.38 | – 1.07 | 0.0269
MRI [A subset of 110 patients was selected for MRI analysis. MRI results were not available for all patients at all time points.]
No. of patients with new Gd-enhancing lesions | 5/32 (16%) | 4/37 (11%) | 0/31 | 0.022
Change in number of T2-weighted lesions, mean (n) | 1.94 (32) | 0.68 (34) | 0.29 (28) | 0.027
NR = not reached within 24 months; MRI = magnetic resonance imaging.

A second randomized, controlled study (Study 2) evaluated mitoxantrone in combination with methylprednisolone (MP) and was conducted in patients with secondary progressive or worsening relapsing-remitting multiple sclerosis who had residual neurological deficit between relapses. All patients had experienced at least two relapses with sequelae or neurological deterioration within the previous 12 months. The average deterioration in EDSS was 2.2 points during the previous 12 months. During the screening period, patients were treated with two monthly doses of 1 g of IV MP and underwent monthly MRI scans. Only patients who developed at least one new Gd-enhancing MRI lesion during the 2-month screening period were eligible for randomization. A total of 42 evaluable patients received monthly treatments of 1 g of IV MP alone (n = 21) or ~12 mg/m^2 of IV mitoxantrone plus 1 g of IV MP (n = 21) (MIT + MP) for 6 months. Patients were evaluated monthly, and study outcome was determined after 6 months. The primary measure of effectiveness in this study was a comparison of the proportion of patients in each treatment group who developed no new Gd-enhancing MRI lesions at 6 months; these MRIs were assessed by a blinded panel. Additional outcomes were measured, including EDSS and number of relapses, but all clinical measures in this trial were assessed by an unblinded treating physician. Five patients, all in the MP alone arm, failed to complete the study due to lack of efficacy.

The results of this trial are displayed in Table 2.

Table 2: Efficacy Results Study 2
Primary Endpoint | MP alone (N = 21) | MIT + MP (N = 21) | p-value
Patients (%) without new Gd-enhancing lesions on MRIs (primary endpoint) [Results at Month 6, not including data for 5 withdrawals in the MP alone group.] | 5 (31%) | 19 (90%) | 0.001
Secondary Endpoints
EDSS change (Month 6 minus baseline) (mean) | – 0.1 | – 1.1 | 0.013
Annualized relapse rate (mean per patient) | 3.0 | 0.7 | 0.003
Patients (%) without relapses | 7 (33%) | 14 (67%) | 0.031
MP = methylprednisolone; MIT + MP = mitoxantrone plus methylprednisolone.

Advanced Hormone-Refractory Prostate Cancer

A multicenter Phase 2 trial of mitoxantrone and low-dose prednisone (M + P) was conducted in 27 symptomatic patients with hormone-refractory prostate cancer. Using NPCP (National Prostate Cancer Project) criteria for disease response, there was one partial responder and 12 patients with stable disease. However, nine patients or 33% achieved a palliative response defined on the basis of reduction in analgesic use or pain intensity.

These findings led to the initiation of a randomized multicenter trial (CCI-NOV22) comparing the effectiveness of (M + P) to low-dose prednisone alone (P). Eligible patients were required to have metastatic or locally advanced disease that had progressed on standard hormonal therapy, a castrate serum testosterone level, and at least mild pain at study entry. Mitoxantrone was administered at a dose of 12 mg/m^2 by short IV infusion every 3 weeks. Prednisone was administered orally at a dose of 5 mg twice a day. Patients randomized to the prednisone arm were crossed over to the M + P arm if they progressed or if they were not improved after a minimum of 6 weeks of therapy with prednisone alone.

A total of 161 patients were randomized, 80 to the M + P arm and 81 to the P arm. The median mitoxantrone dose administered was 12 mg/m^2 per cycle. The median cumulative mitoxantrone dose administered was 73 mg/m^2 (range of 12 to 212 mg/m^2).

A primary palliative response (defined as a 2-point decrease in pain intensity in a 6-point pain scale, associated with stable analgesic use, and lasting a minimum of 6 weeks) was achieved in 29% of patients randomized to M + P compared to 12% of patients randomized to P alone (p = 0.011). Two responders left the study after meeting primary response criterion for two consecutive cycles. For the purposes of this analysis, these two patients were assigned a response duration of zero days. A secondary palliative response was defined as a 50% or greater decrease in analgesic use, associated with stable pain intensity, and lasting a minimum of 6 weeks. An overall palliative response (defined as primary plus secondary responses) was achieved in 38% of patients randomized to M + P compared to 21% of patients randomized to P (p = 0.025).

The median duration of primary palliative response for patients randomized to M + P was 7.6 months compared to 2.1 months for patients randomized to P alone (p = 0.0009). The median duration of overall palliative response for patients randomized to M + P was 5.6 months compared to 1.9 months for patients randomized to P alone (p = 0.0004).

Time to progression was defined as a 1-point increase in pain intensity, or a > 25% increase in analgesic use, or evidence of disease progression on radiographic studies, or requirement for radiotherapy. The median time to progression for all patients randomized to M + P was 4.4 months compared to 2.3 months for all patients randomized to P alone (p = 0.0001). Median time to death was 11.3 months for all patients on the M + P arm compared to 10.8 months for all patients on P alone (p = 0.2324).

Forty-eight patients on the P arm crossed over to receive M + P. Of these, thirty patients had progressed on P, while 18 had stable disease on P. The median cycle of crossover was 5 cycles (range of 2 to 16 cycles). Time trends for pain intensity prior to crossover were significantly worse for patients who crossed over than for those who remained on P alone (p = 0.012). Nine patients (19%) demonstrated a palliative response on M + P after crossover. The median time to death for patients who crossed over to M + P was 12.7 months.

The clinical significance of a fall in prostate-specific antigen (PSA) concentrations after chemotherapy is unclear. On the CCI-NOV22 trial, a PSA fall of 50% or greater for two consecutive follow-up assessments after baseline was reported in 33% of all patients randomized to the M + P arm and 9% of all patients randomized to the P arm. These findings should be interpreted with caution since PSA responses were not defined prospectively. A number of patients were inevaluable for response, and there was an imbalance between treatment arms in the numbers of evaluable patients. In addition, PSA reduction did not correlate precisely with palliative response, the primary efficacy endpoint of this study. For example, among the 26 evaluable patients randomized to the M + P arm who had ≥ 50% reduction in PSA, only 13 had a primary palliative response. Also, among 42 evaluable patients on this arm who did not have this reduction in PSA, 8 nonetheless had a primary palliative response.

Investigators at Cancer and Leukemia Group B (CALGB) conducted a Phase 3 comparative trial of mitoxantrone plus hydrocortisone (M + H) versus hydrocortisone alone (H) in patients with hormone-refractory prostate cancer (CALGB 9182). Eligible patients were required to have metastatic disease that had progressed despite at least one hormonal therapy. Progression at study entry was defined on the basis of progressive symptoms, increases in measurable or osseous disease, or rising PSA levels. Mitoxantrone was administered intravenously at a dose of 14 mg/m^2 every 21 days and hydrocortisone was administered orally at a daily dose of 40 mg. A total of 242 subjects were randomized, 119 to the M + H arm and 123 to the H arm. There were no differences in survival between the two arms, with a median of 11.1 months in the M + H arm and 12 months in the H arm (p = 0.3298).

Using NPCP criteria for response, partial responses were achieved in 10 patients (8.4%) randomized to the M + H arm compared with 2 patients (1.6%) randomized to the H arm (p = 0.018). The median time to progression, defined by NPCP criteria, for patients randomized to the M + H arm was 7.3 months compared to 4.1 months for patients randomized to H alone (p = 0.0654).

Approximately 60% of patients on each arm required analgesics at baseline. Analgesic use was measured in this study using a 5-point scale. The best percent change from baseline in mean analgesic use was -17% for 61 patients with available data on the M + H arm, compared with +17% for 61 patients on H alone (p = 0.014). A time trend analysis for analgesic use in individual patients also showed a trend favoring the M + H arm over H alone but was not statistically significant.

Pain intensity was measured using the Symptom Distress Scale (SDS) Pain Item 2 (a 5-point scale). The best percent change from baseline in mean pain intensity was -14% for 37 patients with available data on the M + H arm, compared with +8% for 38 patients on H alone (p = 0.057). A time trend analysis for pain intensity in individual patients showed no difference between treatment arms.

Acute Nonlymphocytic Leukemia

In two large randomized multicenter trials, remission induction therapy for acute nonlymphocytic leukemia (ANLL) with mitoxantrone 12 mg/m^2 daily for 3 days as a 10-minute intravenous infusion and cytarabine 100 mg/m^2 for 7 days given as a continuous 24-hour infusion was compared with daunorubicin 45 mg/m^2 daily by intravenous infusion for 3 days plus the same dose and schedule of cytarabine used with mitoxantrone. Patients who had an incomplete antileukemic response received a second induction course in which mitoxantrone or daunorubicin was administered for 2 days and cytarabine for 5 days using the same daily dosage schedule. Response rates and median survival information for both the U.S. and international multicenter trials are given in Table 3:

Table 3: Response Rates, Time to Response, and Survival in U.S. and International Trials
Trial | % Complete Response (CR) |  | Median Time to CR (days) |  | Survival (days)
 | MIT | DAUN | MIT | DAUN | MIT | DAUN
U.S. | 63 (62/98) | 53 (54/102) | 35 | 42 | 312 | 237
International | 50 (56/112) | 51 (62/123) | 36 | 42 | 192 | 230
MIT = mitoxantrone + cytarabine
DAUN = daunorubicin + cytarabine

In these studies, two consolidation courses were administered to complete responders on each arm. Consolidation therapy consisted of the same drug and daily dosage used for remission induction, but only 5 days of cytarabine and 2 days of mitoxantrone or daunorubicin were given. The first consolidation course was administered 6 weeks after the start of the final induction course if the patient achieved a complete remission. The second consolidation course was generally administered 4 weeks later. Full hematologic recovery was necessary for patients to receive consolidation therapy. For the U.S. trial, median granulocyte nadirs for patients receiving mitoxantrone + cytarabine for consolidation courses 1 and 2 were 10/mm^3 for both courses, and for those patients receiving daunorubicin + cytarabine nadirs were 170/mm^3 and 260/mm^3, respectively. Median platelet nadirs for patients who received mitoxantrone + cytarabine for consolidation courses 1 and 2 were 17,000/mm^3 and 14,000/mm^3, respectively, and were 33,000/mm^3 and 22,000/mm^3 in courses 1 and 2 for those patients who received daunorubicin + cytarabine. The benefit of consolidation therapy in ANLL patients who achieve a complete remission remains controversial. However, in the only well-controlled prospective, randomized multicenter trials with mitoxantrone in ANLL, consolidation therapy was given to all patients who achieved a complete remission. During consolidation in the U.S. study, two myelosuppression-related deaths occurred in the mitoxantrone arm and one on the daunorubicin arm. However, in the international study there were eight deaths on the mitoxantrone arm during consolidation which were related to the myelosuppression and none on the daunorubicin arm where less myelosuppression occurred.

INDICATIONS AND USAGE

Mitoxantrone is indicated for reducing neurologic disability and/or the frequency of clinical relapses in patients with secondary (chronic) progressive, progressive relapsing, or worsening relapsing-remitting multiple sclerosis (i.e., patients whose neurologic status is significantly abnormal between relapses). Mitoxantrone is not indicated in the treatment of patients with primary progressive multiple sclerosis.

The clinical patterns of multiple sclerosis in the studies were characterized as follows: secondary progressive and progressive relapsing disease were characterized by gradual increasing disability with or without superimposed clinical relapses, and worsening relapsing-remitting disease was characterized by clinical relapses resulting in a step-wise worsening of disability.

Mitoxantrone in combination with corticosteroids is indicated as initial chemotherapy for the treatment of patients with pain related to advanced hormone-refractory prostate cancer.

Mitoxantrone in combination with other approved drug(s) is indicated in the initial therapy of acute nonlymphocytic leukemia (ANLL) in adults. This category includes myelogenous, promyelocytic, monocytic, and erythroid acute leukemias.

CONTRAINDICATIONS

Mitoxantrone is contraindicated in patients who have demonstrated prior hypersensitivity to it.

WARNINGS

WHEN MITOXANTRONE IS USED IN HIGH DOSES (> 14 mg/m^2/d × 3 days) SUCH AS INDICATED FOR THE TREATMENT OF LEUKEMIA, SEVERE MYELOSUPPRESSION WILL OCCUR. THEREFORE, IT IS RECOMMENDED THAT MITOXANTRONE BE ADMINISTERED ONLY BY PHYSICIANS EXPERIENCED IN THE CHEMOTHERAPY OF THIS DISEASE. LABORATORY AND SUPPORTIVE SERVICES MUST BE AVAILABLE FOR HEMATOLOGIC AND CHEMISTRY MONITORING AND ADJUNCTIVE THERAPIES, INCLUDING ANTIBIOTICS.

BLOOD AND BLOOD PRODUCTS MUST BE AVAILABLE TO SUPPORT PATIENTS DURING THE EXPECTED PERIOD OF MEDULLARY HYPOPLASIA AND SEVERE MYELOSUPPRESSION. PARTICULAR CARE SHOULD BE GIVEN TO ASSURING FULL HEMATOLOGIC RECOVERY BEFORE UNDERTAKING CONSOLIDATION THERAPY (IF THIS TREATMENT IS USED) AND PATIENTS SHOULD BE MONITORED CLOSELY DURING THIS PHASE. MITOXANTRONE ADMINISTERED AT ANY DOSE CAN CAUSE MYELOSUPPRESSION.

CONTAINS SODIUM METABISULFITE, A SULFITE THAT MAY CAUSE ALLERGIC-TYPE REACTIONS INCLUDING ANAPHYLACTIC SYMPTOMS AND LIFE-THREATENING OR LESS SEVERE ASTHMATIC EPISODES IN CERTAIN SUSCEPTIBLE PEOPLE. THE OVERALL PREVALENCE OF SULFITE SENSITIVITY IN THE GENERAL POPULATION IS UNKNOWN AND PROBABLY LOW. SULFITE SENSITIVITY IS SEEN MORE FREQUENTLY IN ASTHMATIC THAN IN NONASTHMATIC PEOPLE.

General

Patients with preexisting myelosuppression as the result of prior drug therapy should not receive mitoxantrone unless it is felt that the possible benefit from such treatment warrants the risk of further medullary suppression.

The safety of Mitoxantrone Injection, USP (concentrate) in patients with hepatic insufficiency is not established (see CLINICAL PHARMACOLOGY).

Safety for use by routes other than intravenous administration has not been established.

Mitoxantrone is not indicated for subcutaneous, intramuscular, or intra-arterial injection. There have been reports of local/regional neuropathy, some irreversible, following intra-arterial injection.

Mitoxantrone must not be given by intrathecal injection. There have been reports of neuropathy and neurotoxicity, both central and peripheral, following intrathecal injection. These reports have included seizures leading to coma and severe neurologic sequelae, and paralysis with bowel and bladder dysfunction.

Topoisomerase II inhibitors, including mitoxantrone, have been associated with the development of secondary acute myeloid leukemia and myelosuppression.

Cardiac Effects

Because of the possible danger of cardiac effects in patients previously treated with daunorubicin or doxorubicin, the benefit-to-risk ratio of mitoxantrone therapy in such patients should be determined before starting therapy.

Functional cardiac changes including decreases in left ventricular ejection fraction (LVEF) and irreversible congestive heart failure can occur with mitoxantrone. Cardiac toxicity may be more common in patients with prior treatment with anthracyclines, prior mediastinal radiotherapy, or with preexisting cardiovascular disease. Such patients should have regular cardiac monitoring of LVEF from the initiation of therapy. Cancer patients who received cumulative doses of 140 mg/m^2 either alone or in combination with other chemotherapeutic agents had a cumulative 2.6% probability of clinical congestive heart failure. In comparative oncology trials, the overall cumulative probability rate of moderate or severe decreases in LVEF at this dose was 13%.

Multiple Sclerosis

Changes in cardiac function may occur in patients with multiple sclerosis treated with mitoxantrone. In one controlled trial (Study 1, see CLINICAL TRIALS, Multiple Sclerosis), two patients (2%) of 127 receiving mitoxantrone, one receiving a 5 mg/m^2 dose and the other receiving the 12 mg/m^2 dose, had LVEF values that decreased to below 50%. An additional patient receiving 12 mg/m^2, who did not have LVEF measured, had a decrease in another echocardiographic measurement of ventricular function (fractional shortening) that led to discontinuation from the trial (see ADVERSE REACTIONS, Multiple Sclerosis). There were no reports of congestive heart failure in either controlled trial.

MS patients should be assessed for cardiac signs and symptoms by history, physical examination, ECG, and quantitative LVEF evaluation using appropriate methodology (ex. Echocardiogram, MUGA, MRI, etc.) prior to the start of mitoxantrone therapy. MS patients with a baseline LVEF below the lower limit of normal should not be treated with mitoxantrone. Subsequent LVEF and ECG evaluations are recommended if signs or symptoms of congestive heart failure develop and prior to every dose administered to MS patients. Mitoxantrone should not be administered to MS patients who experience a reduction in LVEF to below the lower limit of normal, to those who experience a clinically significant reduction in LVEF, or to those who have received a cumulative lifetime dose of 140 mg/m^2. MS patients should have yearly quantitative LVEF evaluation after stopping mitoxantrone to monitor for late-occurring cardiotoxicity.

Leukemia

Acute congestive heart failure may occasionally occur in patients treated with mitoxantrone for ANLL. In first-line comparative trials of mitoxantrone + cytarabine vs daunorubicin + cytarabine in adult patients with previously untreated ANLL, therapy was associated with congestive heart failure in 6.5% of patients on each arm. A causal relationship between drug therapy and cardiac effects is difficult to establish in this setting since myocardial function is frequently depressed by the anemia, fever and infection, and hemorrhage that often accompany the underlying disease.

Hormone-Refractory Prostate Cancer

Functional cardiac changes such as decreases in LVEF and congestive heart failure may occur in patients with hormone-refractory prostate cancer treated with mitoxantrone. In a randomized comparative trial of mitoxantrone plus low-dose prednisone vs low-dose prednisone, 7 of 128 patients (5.5%) treated with mitoxantrone had a cardiac event defined as any decrease in LVEF below the normal range, congestive heart failure (n = 3), or myocardial ischemia. Two patients had a prior history of cardiac disease. The total mitoxantrone dose administered to patients with cardiac effects ranged from > 48 to 212 mg/m^2.

Among 112 patients evaluable for safety on the mitoxantrone + hydrocortisone arm of the CALGB trial, 18 patients (19%) had a reduction in cardiac function, 5 patients (5%) had cardiac ischemia, and 2 patients (2%) experienced pulmonary edema. The range of total mitoxantrone doses administered to these patients is not available.

Pregnancy

Mitoxantrone may cause fetal harm when administered to a pregnant woman. Women of childbearing potential should be advised to avoid becoming pregnant. Mitoxantrone is considered a potential human teratogen because of its mechanism of action and the developmental effects demonstrated by related agents. Treatment of pregnant rats during the organogenesis period of gestation was associated with fetal growth retardation at doses ≥0.1 mg/kg/day (0.01 times the recommended human dose on a mg/m^2 basis). When pregnant rabbits were treated during organogenesis, an increased incidence of premature delivery was observed at doses ≥0.1 mg/kg/day (0.01 times the recommended human dose on a mg/m^2 basis). No teratogenic effects were observed in these studies, but the maximum doses tested were well below the recommended human dose (0.02 and 0.05 times in rats and rabbits, respectively, on a mg/m^2 basis). There are no adequate and well-controlled studies in pregnant women. Women with multiple sclerosis who are biologically capable of becoming pregnant should have a pregnancy test prior to each dose, and the results should be known prior to administration of the drug. If this drug is used during pregnancy or if the patient becomes pregnant while taking this drug, the patient should be apprised of the potential risk to the fetus.

Secondary Leukemia

Mitoxantrone therapy increases the risk of developing secondary leukemia in patients with cancer and in patients with multiple sclerosis.

In a study of patients with prostate cancer, acute myeloid leukemia occurred in 1% (5/487) of mitoxantrone-treated patients versus no cases in the control group (0/496) not receiving mitoxantrone at 4.7 years followup.

In a prospective, open-label, tolerability and safety monitoring study of mitoxantrone treated MS patients followed for up to five years (median of 2.8 years), leukemia occurred in 0.6% (3/509) of patients. Publications describe leukemia risk of 0.25% to 2.8% in cohorts of patients with MS treated with mitoxantrone and followed for varying periods of time. This leukemia risk exceeds the risk of leukemia in the general population. The most commonly reported types were acute promyelocytic leukemia and acute myelocytic leukemia.

In 1774 patients with breast cancer who received mitoxantrone concomitantly with other cytotoxic agents and radiotherapy, the cumulative risk of developing treatment-related acute myeloid leukemia was estimated as 1.1% and 1.6% at 5 and 10 years, respectively. The second largest report involved 449 patients with breast cancer treated with mitoxantrone, usually in combination with radiotherapy and/or other cytotoxic agents. In this study, the cumulative probability of developing secondary leukemia was estimated to be 2.2% at 4 years.

Secondary acute myeloid leukemia has also been reported in cancer patients treated with anthracyclines. Mitoxantrone is an anthracenedione, a related drug. The occurrence of secondary leukemia is more common when anthracyclines are given in combination with DNA-damaging antineoplastic agents, when patients have been heavily pretreated with cytotoxic drugs, or when doses of anthracyclines have been escalated.

Symptoms of acute leukemia may include excessive bruising, bleeding, and recurrent infections.

PRECAUTIONS

General

Therapy with mitoxantrone should be accompanied by close and frequent monitoring of hematologic and chemical laboratory parameters, as well as frequent patient observation.

Systemic infections should be treated concomitantly with or just prior to commencing therapy with mitoxantrone.

Information for Patients

See FDA-approved patient labeling (MEDICATION GUIDE).

Inform patients of the availability of a Medication Guide and instruct them to read the Medication Guide prior to initiating treatment with MitoXANTRONE and prior to each infusion. Review the MitoXANTRONE Medication Guide with every patient prior to initiation of treatment and periodically during treatment. Instruct patients that MitoXANTRONE should be taken only as prescribed.

Advise patients that MitoXANTRONE can cause myelosuppression and inform patients of the signs and symptoms of myelosuppression. Advise patients that MitoXANTRONE can cause congestive heart failure that may lead to death even in people who have never had heart problems before, and inform patients of the signs and symptoms of congestive heart failure. Advise patients receiving MitoXANTRONE to treat multiple sclerosis that they should receive cardiac monitoring prior to each MitoXANTRONE dose and yearly after stopping MitoXANTRONE.

MitoXANTRONE may impart a blue-green color to the urine for 24 hours after administration, and patients should be advised to expect this during therapy. Bluish discoloration of the sclera may also occur.

Laboratory Tests

A complete blood count, including platelets, should be obtained prior to each course of mitoxantrone and in the event that signs and symptoms of infection develop. Liver function tests should also be performed prior to each course of therapy. Mitoxantrone therapy in multiple sclerosis patients with abnormal liver function tests is not recommended because mitoxantrone clearance is reduced by hepatic impairment and no laboratory measurement can predict drug clearance and dose adjustments.

In leukemia treatment, hyperuricemia may occur as a result of rapid lysis of tumor cells by mitoxantrone. Serum uric acid levels should be monitored and hypouricemic therapy instituted prior to the initiation of antileukemic therapy.

Women with multiple sclerosis who are biologically capable of becoming pregnant, even if they are using birth control, should have a pregnancy test, and the results should be known, before receiving each dose of mitoxantrone (see WARNINGS, Pregnancy).

Carcinogenesis, Mutagenesis, Impairment of Fertility

Carcinogenesis

Intravenous treatment of rats and mice, once every 21 days for 24 months, with mitoxantrone resulted in an increased incidence of fibroma and external auditory canal tumors in rats at a dose of 0.03 mg/kg (0.02 fold the recommended human dose, on a mg/m^2 basis), and hepatocellular adenoma in male mice at a dose of 0.1 mg/kg (0.03 fold the recommended human dose, on a mg/m^2 basis). Intravenous treatment of rats, once every 21 days for 12 months with mitoxantrone resulted in an increased incidence of external auditory canal tumors in rats at a dose of 0.3 mg/kg (0.15 fold the recommended human dose, on a mg/m^2 basis).

Mutagenesis

Mitoxantrone was clastogenic in the in vivo rat bone marrow assay. Mitoxantrone was also clastogenic in two in vitro assays; it induced DNA damage in primary rat hepatocytes and sister chromatid exchanges in Chinese hamster ovary cells. Mitoxantrone was mutagenic in bacterial and mammalian test systems (Ames/Salmonella and E. coli and L5178Y TK+/-mouse lymphoma).

Drug Interactions

Mitoxantrone and its metabolites are excreted in bile and urine, but it is not known whether the metabolic or excretory pathways are saturable, may be inhibited or induced, or if mitoxantrone and its metabolites undergo enterohepatic circulation. To date, post-marketing experience has not revealed any significant drug interactions in patients who have received mitoxantrone for treatment of cancer. Information on drug interactions in patients with multiple sclerosis is limited.

Following concurrent administration of mitoxantrone with corticosteroids, no evidence of drug interactions has been observed.

Special Populations

Hepatic Impairment

Patients with multiple sclerosis who have hepatic impairment should ordinarily not be treated with mitoxantrone. Mitoxantrone should be administered with caution to other patients with hepatic impairment. In patients with severe hepatic impairment, the AUC is more than three times greater than the value observed in patients with normal hepatic function.

Pregnancy

(see WARNINGS).

Nursing Mothers

Mitoxantrone is excreted in human milk and significant concentrations (18 ng/mL) have been reported for 28 days after the last administration. Because of the potential for serious adverse reactions in infants from mitoxantrone, breast feeding should be discontinued before starting treatment.

Pediatric Use

Safety and effectiveness in pediatric patients have not been established.

Geriatric Use

Multiple Sclerosis

Clinical studies of mitoxantrone did not include sufficient numbers of patients aged 65 and over to determine whether they respond differently from younger patients. Other reported clinical experience has not identified differences in responses between the elderly and younger patients.

Hormone-Refractory Prostate Cancer

One hundred forty-six patients aged 65 and over and 52 younger patients (<65 years) have been treated with mitoxantrone in controlled clinical studies. These studies did not include sufficient numbers of younger patients to determine whether they respond differently from older patients. However, greater sensitivity of some older individuals cannot be ruled out.

Acute Nonlymphocytic Leukemia

Although definitive studies with mitoxantrone have not been performed in geriatric patients with ANLL, toxicity may be more frequent in the elderly. Elderly patients are more likely to have age-related comorbidities due to disease or disease therapy.

ADVERSE REACTIONS

Multiple Sclerosis

Mitoxantrone has been administered to 149 patients with multiple sclerosis in two randomized clinical trials, including 21 patients who received mitoxantrone in combination with corticosteroids.

In Study 1, the proportion of patients who discontinued treatment due to an adverse event was 9.7% (n = 6) in the 12 mg/m^2 mitoxantrone arm (leukopenia, depression, decreased LV function, bone pain and emesis, renal failure, and one discontinuation to prevent future complications from repeated urinary tract infections) compared to 3.1% (n = 2) in the placebo arm (hepatitis and myocardial infarction). The following clinical adverse experiences were significantly more frequent in the mitoxantrone groups: nausea, alopecia, urinary tract infection, and menstrual disorders, including amenorrhea.

Table 4a summarizes clinical adverse events of all intensities occurring in ≥5% of patients in either dose group of mitoxantrone and that were numerically greater on drug than on placebo in Study 1. The majority of these events were of mild to moderate intensity, and nausea was the only adverse event that occurred with severe intensity in more than one patient (three patients [5%] in the 12 mg/m^2 group). Of note, alopecia consisted of mild hair thinning.

Two of the 127 patients treated with mitoxantrone in Study 1 had decreased LVEF to below 50% at some point during the 2 years of treatment. An additional patient receiving 12 mg/m^2 did not have LVEF measured, but had another echocardiographic measure of ventricular function (fractional shortening) that led to discontinuation from the study.

Table 4a: Adverse Events of Any Intensity Occurring in ≥ 5% of Patients on Any Dose of Mitoxantrone and That Were Numerically Greater Than in the Placebo Group Study 1
 | Percent of Patients
Preferred Term | Placebo (N = 64) | 5 mg/m^2 Mitoxantrone (N = 65) | 12 mg/m^2 Mitoxantrone (N = 62)
Nausea | 20 | 55 | 76
Alopecia | 31 | 38 | 61
Menstrual disorder [Percentage of female patients.] | 26 | 51 | 61
Amenorrhea | 3 | 28 | 43
Upper respiratory tract infection | 52 | 51 | 53
Urinary tract infection | 13 | 29 | 32
Stomatitis | 8 | 15 | 19
Arrhythmia | 8 | 6 | 18
Diarrhea | 11 | 25 | 16
Urine abnormal | 6 | 5 | 11
ECG abnormal | 3 | 5 | 11
Constipation | 6 | 14 | 10
Back pain | 5 | 6 | 8
Sinusitis | 2 | 3 | 6
Headache | 5 | 6 | 6

The proportion of patients experiencing any infection during Study 1 was 67% for the placebo group, 85% for the 5 mg/m^2 group, and 81% for the 12 mg/m^2 group. However, few of these infections required hospitalization: one placebo patient (tonsillitis), three 5 mg/m^2 patients (enteritis, urinary tract infection, viral infection), and four 12 mg/m^2 patients (tonsillitis, urinary tract infection [two], endometritis).

Table 4b summarizes laboratory abnormalities that occurred in ≥ 5% of patients in either mitoxantrone dose group, and that were numerically more frequent than in the placebo group.

Table 4b: Laboratory Abnormalities Occurring in ≥ 5% of Patients [Assessed using World Health Organization (WHO) toxicity criteria.] on Either Dose of Mitoxantrone and That Were More Frequent Than in the Placebo Group Study 1
 | Percent of Patients
Event | Placebo (N = 64) | 5 mg/m^2 Mitoxantrone (N = 65) | 12 mg/m^2 Mitoxantrone (N = 62)
Leukopenia [< 4000 cells/mm^3] | 0 | 9 | 19
Gamma-GT increased | 3 | 3 | 15
SGOT increased | 8 | 9 | 8
Granulocytopenia [< 2000 cells/mm^3] | 2 | 6 | 6
Anemia | 2 | 9 | 6
SGPT increased | 3 | 6 | 5

There was no difference among treatment groups in the incidence or severity of hemorrhagic events.

In Study 2, mitoxantrone was administered once a month. Clinical adverse events most frequently reported in the mitoxantrone group included amenorrhea (53% of female patients), alopecia (33% of patients), nausea (29% of patients), and asthenia (24% of patients). Tables 5a and 5b respectively summarize adverse events and laboratory abnormalities occurring in > 5% of patients in the mitoxantrone group and numerically more frequent than in the control group.

Table 5a: Adverse Events of Any Intensity Occurring in > 5% of Patients [Assessed using National Cancer Institute (NCI) common toxicity criteria.] in the Mitoxantrone Group and Numerically More Frequent Than in the Control Group Study 2
 | Percent of Patients
Event | MP (N = 21) | M + MP (N = 21)
Amenorrhea [Percentage of female patients.] | 0 | 53
Alopecia | 0 | 33
Nausea | 0 | 29
Asthenia | 0 | 24
Pharyngitis/throat infection | 5 | 19
Gastralgia/stomach burn/epigastric pain | 5 | 14
Aphthosis | 0 | 10
Cutaneous mycosis | 0 | 10
Rhinitis | 0 | 10
Menorrhagia | 0 | 7
M = mitoxantrone, MP = methylprednisolone

Table 5b: Laboratory Abnormalities Occurring in > 5% of Patients [Assessed using National Cancer Institute (NCI) common toxicity criteria.] in the Mitoxantrone Group and Numerically More Frequent Than in the Control Group Study 2
 | Percent of Patients
Event | MP (N = 21) | M + MP (N = 21)
WBC low [< 4000 cells/mm^3] | 14 | 100
ANC low [< 1500 cells/mm^3] | 10 | 100
Lymphocytes low | 43 | 95
Hemoglobin low | 48 | 43
Platelets low [< 100,000 cells/mm^3] | 0 | 33
SGOT high | 5 | 15
SGPT high | 10 | 15
Glucose high | 5 | 10
Potassium low | 0 | 10
M = mitoxantrone, MP = methylprednisolone

Leukopenia and neutropenia were reported in the M + MP group (see Table 5b).

Neutropenia occurred within 3 weeks after mitoxantrone administration and was always reversible. Only mild to moderate intensity infections were reported in 9 of 21 patients in the M + MP group and in 3 of 21 patients in the MP group; none of these required hospitalization. There was no difference among treatment groups in the incidence or severity of hemorrhagic events. There were no withdrawals from Study 2 for safety reasons.

Leukemia

Mitoxantrone has been studied in approximately 600 patients with acute non-lymphocytic leukemia (ANLL). Table 6 represents the adverse reaction experience in the large U.S. comparative study of mitoxantrone + cytarabine vs daunorubicin + cytarabine. Experience in the large international study was similar. A much wider experience in a variety of other tumor types revealed no additional important reactions other than cardiomyopathy (see WARNINGS). It should be appreciated that the listed adverse reaction categories include overlapping clinical symptoms related to the same condition, e.g., dyspnea, cough and pneumonia. In addition, the listed adverse reactions cannot all necessarily be attributed to chemotherapy as it is often impossible to distinguish effects of the drug and effects of the underlying disease. It is clear, however, that the combination of mitoxantrone + cytarabine was responsible for nausea and vomiting, alopecia, mucositis/stomatitis, and myelosuppression.

Table 6 summarizes adverse reactions occurring in patients treated with mitoxantrone + cytarabine in comparison with those who received daunorubicin + cytarabine for therapy of ANLL in a large multicenter randomized prospective U.S. trial.

Adverse reactions are presented as major categories and selected examples of clinically significant subcategories.

Table 6: Adverse Events Occurring in ANLL Patients Receiving Mitoxantrone or Daunorubicin
 | Induction [% pts entering induction] |  | Consolidation [% pts entering induction]
Event | MIT N = 102 | DAUN N = 102 | MIT N = 55 | DAUN N = 49
Cardiovascular | 26 | 28 | 11 | 24
CHF | 5 | 6 | 0 | 0
Arrhythmias | 3 | 3 | 4 | 4
Bleeding | 37 | 41 | 20 | 6
GI | 16 | 12 | 2 | 2
Petechiae/ecchymoses | 7 | 9 | 11 | 2
Gastrointestinal | 88 | 85 | 58 | 51
Nausea/vomiting | 72 | 67 | 31 | 31
Diarrhea | 47 | 47 | 18 | 8
Abdominal pain | 15 | 9 | 9 | 4
Mucositis/stomatitis | 29 | 33 | 18 | 8
Hepatic | 10 | 11 | 14 | 2
Jaundice | 3 | 8 | 7 | 0
Infections | 66 | 73 | 60 | 43
UTI | 7 | 2 | 7 | 2
Pneumonia | 9 | 7 | 9 | 0
Sepsis | 34 | 36 | 31 | 18
Fungal infections | 15 | 13 | 9 | 6
Renal failure | 8 | 6 | 0 | 2
Fever | 78 | 71 | 24 | 18
Alopecia | 37 | 40 | 22 | 16
Pulmonary | 43 | 43 | 24 | 14
Cough | 13 | 9 | 9 | 2
Dyspnea | 18 | 20 | 6 | 0
CNS | 30 | 30 | 34 | 35
Seizures | 4 | 4 | 2 | 8
Headache | 10 | 9 | 13 | 8
Eye | 7 | 6 | 2 | 4
Conjunctivitis | 5 | 1 | 0 | 0
MIT = mitoxantrone, DAUN = daunorubicin.

Hormone-Refractory Prostate Cancer

Detailed safety information is available for a total of 353 patients with hormone-refractory prostate cancer treated with mitoxantrone, including 274 patients who received mitoxantrone in combination with corticosteroids.

Table 7 summarizes adverse reactions of all grades occurring in ≥5% of patients in Trial CCI-NOV22.

Table 7: Adverse Events of Any Intensity Occurring in ≥5% of Patients Trial CCI-NOV22
Event | M + P (n = 80) % | P (n = 81) %
Nausea | 61 | 35
Fatigue | 39 | 14
Alopecia | 29 | 0
Anorexia | 25 | 6
Constipation | 16 | 14
Dyspnea | 11 | 5
Nail bed changes | 11 | 0
Edema | 10 | 4
Systemic infection | 10 | 7
Mucositis | 10 | 0
UTI | 9 | 4
Emesis | 9 | 5
Pain | 8 | 9
Fever | 6 | 3
Hemorrhage/bruise | 6 | 1
Anemia | 5 | 3
Cough | 5 | 0
Decreased LVEF | 5 | 0
Anxiety/depression | 5 | 3
Dyspepsia | 5 | 6
Skin infection | 5 | 3
Blurred vision | 3 | 5
M = mitoxantrone, P = prednisone.
No nonhematologic adverse events of Grade 3/4 were seen in > 5% of patients.

Table 8 summarizes adverse events of all grades occurring in ≥ 5% of patients in Trial CALGB 9182.

Table 8: Adverse Events of Any Intensity Occurring in ≥ 5% of Patients. Trial CALGB 9182
 | M + H (n = 112) |  | H (n = 113)
Event | n | % | n | %
Decreased WBC | 96 | 87 | 4 | 4
Abnormal granulocytes/bands | 88 | 79 | 3 | 3
Decreased hemoglobin | 83 | 75 | 42 | 39
Abnormal lymphocytes count | 78 | 72 | 27 | 25
Pain | 45 | 41 | 44 | 39
Abnormal platelet count | 43 | 39 | 8 | 7
Abnormal alkaline phosphatase | 41 | 37 | 42 | 38
Malaise/fatigue | 37 | 34 | 16 | 14
Hyperglycemia | 33 | 31 | 32 | 30
Edema | 31 | 30 | 15 | 14
Nausea | 28 | 26 | 9 | 8
Anorexia | 24 | 22 | 16 | 14
Abnormal BUN | 24 | 22 | 22 | 20
Abnormal transaminase | 22 | 20 | 16 | 14
Alopecia | 20 | 20 | 1 | 1
Abnormal cardiac function | 19 | 18 | 0 | 0
Infection | 18 | 17 | 4 | 4
Weight loss | 18 | 17 | 13 | 12
Dyspnea | 16 | 15 | 9 | 8
Diarrhea | 16 | 14 | 4 | 4
Fever in absence of infection | 15 | 14 | 7 | 6
Weight gain | 15 | 14 | 16 | 15
Abnormal creatinine | 14 | 13 | 11 | 10
Other gastrointestinal | 13 | 14 | 11 | 11
Vomiting | 12 | 11 | 6 | 5
Other neurologic | 11 | 11 | 5 | 5
Hypocalcemia | 10 | 10 | 5 | 5
Hematuria | 9 | 11 | 5 | 6
Hyponatremia | 9 | 9 | 3 | 3
Sweats | 9 | 9 | 2 | 2
Other liver | 8 | 8 | 8 | 8
Stomatitis | 8 | 8 | 1 | 1
Cardiac dysrhythmia | 7 | 7 | 3 | 3
Hypokalemia | 7 | 7 | 4 | 4
Neuro/constipation | 7 | 7 | 2 | 2
Neuro/motor disorder | 7 | 7 | 3 | 3
Neuro/mood disorder | 6 | 6 | 2 | 2
Skin disorder | 6 | 6 | 4 | 4
Cardiac ischemia | 5 | 5 | 1 | 1
Chills | 5 | 5 | 0 | 0
Hemorrhage | 5 | 5 | 3 | 3
Myalgias/arthralgias | 5 | 5 | 3 | 3
Other kidney/bladder | 5 | 5 | 3 | 3
Other endocrine | 5 | 6 | 3 | 4
Other pulmonary | 5 | 5 | 3 | 3
Hypertension | 4 | 4 | 5 | 5
Impotence/libido | 4 | 7 | 2 | 3
Proteinuria | 4 | 6 | 2 | 3
Sterility | 3 | 5 | 2 | 3
M = mitoxantrone, H = hydrocortisone

General

Allergic Reaction

Hypotension, urticaria, dyspnea, and rashes have been reported occasionally. Anaphylaxis/anaphylactoid reactions have been reported rarely.

Cutaneous

Extravasation at the infusion site has been reported, which may result in erythema, swelling, pain, burning, and/or blue discoloration of the skin. Extravasation can result in tissue necrosis with resultant need for debridement and skin grafting. Phlebitis has also been reported at the site of the infusion.

Hematologic

Topoisomerase II inhibitors, including mitoxantrone, in combination with other antineoplastic agents or alone, have been associated with the development of acute leukemia (see WARNINGS).

Leukemia

Myelosuppression is rapid in onset and is consistent with the requirement to produce significant marrow hypoplasia in order to achieve a response in acute leukemia. The incidences of infection and bleeding seen in the U.S. trial are consistent with those reported for other standard induction regimens.

Hormone-Refractory Prostate Cancer

In a randomized study where dose escalation was required for neutrophil counts greater than 1000/mm^3, Grade 4 neutropenia (ANC < 500/mm^3) was observed in 54% of patients treated with mitoxantrone + low-dose prednisone. In a separate randomized trial where patients were treated with 14 mg/m^2, Grade 4 neutropenia in 23% of patients treated with mitoxantrone + hydrocortisone was observed. Neutropenic fever/infection occurred in 11% and 10% of patients receiving mitoxantrone + corticosteroids, respectively, on the two trials. Platelets < 50,000/mm^3 were noted in 4% and 3% of patients receiving mitoxantrone + corticosteroids on these trials, and there was one patient death on mitoxantrone + hydrocortisone due to intracranial hemorrhage after a fall.

Gastrointestinal

Nausea and vomiting occurred acutely in most patients and may have contributed to reports of dehydration, but were generally mild to moderate and could be controlled through the use of antiemetics. Stomatitis/mucositis occurred within 1 week of therapy.

Cardiovascular

Congestive heart failure, tachycardia, EKG changes including arrhythmias, chest pain, and asymptomatic decreases in left ventricular ejection fraction have occurred. (See WARNINGS)

Pulmonary

Interstitial pneumonitis has been reported in cancer patients receiving combination chemotherapy that included mitoxantrone.

OVERDOSAGE

There is no known specific antidote for mitoxantrone. Accidental overdoses have been reported. Four patients receiving 140 to 180 mg/m^2 as a single bolus injection died as a result of severe leukopenia with infection. Hematologic support and antimicrobial therapy may be required during prolonged periods of severe myelosuppression.

Although patients with severe renal failure have not been studied, mitoxantrone is extensively tissue bound and it is unlikely that the therapeutic effect or toxicity would be mitigated by peritoneal or hemodialysis.

DOSAGE AND ADMINISTRATION

(See also WARNINGS)

Multiple Sclerosis

The recommended dosage of mitoxantrone is 12 mg/m^2 given as a short (approximately 5 to 15 minutes) intravenous infusion every 3 months. Left ventricular ejection fraction (LVEF) should be evaluated by echocardiogram or MUGA prior to administration of the initial dose of mitoxantrone and all subsequent doses. In addition, LVEF evaluations are recommended if signs or symptoms of congestive heart failure develop at any time during treatment with mitoxantrone. Mitoxantrone should not be administered to multiple sclerosis patients with an LVEF <50%, with a clinically significant reduction in LVEF, or to those who have received a cumulative lifetime dose of ≥140 mg/m^2. Complete blood counts, including platelets, should be monitored prior to each course of mitoxantrone and in the event that signs or symptoms of infection develop. Mitoxantrone generally should not be administered to multiple sclerosis patients with neutrophil counts less than 1500 cells/mm^3. Liver function tests should also be monitored prior to each course. Mitoxantrone therapy in multiple sclerosis patients with abnormal liver function tests is not recommended because mitoxantrone clearance is reduced by hepatic impairment and no laboratory measurement can predict drug clearance and dose adjustments.

Women with multiple sclerosis who are biologically capable of becoming pregnant, even if they are using birth control, should have a pregnancy test, and the results should be known, before receiving each dose of mitoxantrone (see WARNINGS, Pregnancy).

Hormone-Refractory Prostate Cancer

Based on data from two Phase 3 comparative trials of mitoxantrone plus corticosteroids versus corticosteroids alone, the recommended dosage of mitoxantrone is 12 to 14 mg/m^2 given as a short intravenous infusion every 21 days.

Combination Initial Therapy for ANLL in Adults

For induction, the recommended dosage is 12 mg/m^2 of mitoxantrone daily on Days 1 to 3 given as an intravenous infusion, and 100 mg/m^2 of cytarabine for 7 days given as a continuous 24-hour infusion on Days 1 to 7.

Most complete remissions will occur following the initial course of induction therapy. In the event of an incomplete antileukemic response, a second induction course may be given. Mitoxantrone should be given for 2 days and cytarabine for 5 days using the same daily dosage levels.

If severe or life-threatening nonhematologic toxicity is observed during the first induction course, the second induction course should be withheld until toxicity resolves.

Consolidation therapy which was used in two large randomized multicenter trials consisted of mitoxantrone, 12 mg/m^2 given by intravenous infusion daily on Days 1 and 2 and cytarabine, 100 mg/m^2 for 5 days given as a continuous 24-hour infusion on Days 1 to 5. The first course was given approximately 6 weeks after the final induction course; the second was generally administered 4 weeks after the first. Severe myelosuppression occurred. (See CLINICAL PHARMACOLOGY)

Hepatic Impairment

For patients with hepatic impairment, there is at present no laboratory measurement that allows for dose adjustment recommendations. (See CLINICAL PHARMACOLOGY, Special Populations, Hepatic Impairment)

Preparation and Administration Precautions

MITOXANTRONE INJECTION, USP (CONCENTRATE) MUST BE DILUTED PRIOR TO USE.

Parenteral drug products should be inspected visually for particulate matter and discoloration prior to administration whenever solution and container permit. The dose of mitoxantrone should be diluted to at least 50 mL with either 0.9% Sodium Chloride Injection (USP) or 5% Dextrose Injection (USP). Mitoxantrone Injection, USP (concentrate) may be further diluted into Dextrose 5% in Water, Normal Saline or Dextrose 5% with Normal Saline and used immediately. DO NOT FREEZE.

Mitoxantrone should not be mixed in the same infusion as heparin since a precipitate may form. Because specific compatibility data are not available, it is recommended that mitoxantrone not be mixed in the same infusion with other drugs. The diluted solution should be introduced slowly into the tubing as a freely running intravenous infusion of 0.9% Sodium Chloride Injection (USP) or 5% Dextrose Injection (USP) over a period of not less than 3 minutes. Unused infusion solutions should be discarded immediately in an appropriate fashion. In the case of multiple-dose use, after penetration of the stopper, the remaining portion of the undiluted Mitoxantrone Injection, USP concentrate should be stored not longer than 7 days between 15° to 25°C (59° to 77°F) or 14 days under refrigeration. DO NOT FREEZE. CONTAINS NO PRESERVATIVE.

Care in the administration of mitoxantrone will reduce the chance of extravasation. Mitoxantrone should be administered into the tubing of a freely running intravenous infusion of 0.9% Sodium Chloride Injection, USP or 5% Dextrose Injection, USP. The tubing should be attached to a Butterfly needle or other suitable device and inserted preferably into a large vein. If possible, avoid veins over joints or in extremities with compromised venous or lymphatic drainage. Care should be taken to avoid extravasation at the infusion site and to avoid contact of mitoxantrone with the skin, mucous membranes, or eyes. MITOXANTRONE SHOULD NOT BE ADMINISTERED SUBCUTANEOUSLY. If any signs or symptoms of extravasation have occurred, including burning, pain, pruritis, erythema, swelling, blue discoloration, or ulceration, the injection or infusion should be immediately terminated and restarted in another vein. During intravenous administration of mitoxantrone extravasation may occur with or without an accompanying stinging or burning sensation even if blood returns well on aspiration of the infusion needle. If it is known or suspected that subcutaneous extravasation has occurred, it is recommended that intermittent ice packs be placed over the area of extravasation and that the affected extremity be elevated. Because of the progressive nature of extravasation reactions, the area of injection should be frequently examined and surgery consultation obtained early if there is any sign of a local reaction.

Skin accidentally exposed to mitoxantrone should be rinsed copiously with warm water and if the eyes are involved, standard irrigation techniques should be used immediately. The use of goggles, gloves, and protective gowns is recommended during preparation and administration of the drug.

Procedures for proper handling and disposal of anticancer drugs should be considered. Several guidelines on this subject have been published.^1–4 There is no general agreement that all of the procedures recommended in the guidelines are necessary or appropriate.

REFERENCES

1. NIOSH Alert: Preventing occupational exposures to antineoplastic and other hazardous drugs in healthcare settings. 2004. U.S. Department of Health and Human Services, Public Health Service, Centers for Disease Control and Prevention, National Institute for Occupational Safety and Health, DHHS (NIOSH) Publication No. 2004-165.
2. OSHA Technical Manual, TED 1-0.15A, Section VI: Chapter 2. Controlling Occupational Exposure to Hazardous Drugs. OSHA, 1999. http://www.osha.gov/dts/osta/otm_vi_2.html.
3. American Society of Health-System Pharmacists. (2006) ASHP Guidelines on Handling Hazardous Drugs.
4. Polovich, M., White, J.M., & Kelleher, L.O. (eds.) 2005. Chemotherapy and biotherapy guidelines and recommendations for practice (2nd ed.) Pittsburgh, PA: Oncology Nursing Society.

HOW SUPPLIED

Mitoxantrone Injection, USP (concentrate) is a sterile aqueous solution containing mitoxantrone hydrochloride at a concentration equivalent to 2 mg mitoxantrone free base per mL supplied in vials for multiple-dose use as follows:

Unit of Sale | Concentration
NDC 61703-343-18 Carton containing 1 multiple-dose vial | 20 mg/10 mL (2 mg/ mL)
NDC 61703-343-65 Carton containing 1 multiple-dose vial | 25 mg/12.5 mL (2 mg/ mL)
NDC 61703-343-66 Carton containing 1 multiple-dose vial | 30 mg/15 mL (2 mg/ mL)

STORAGE AND HANDLING

Mitoxantrone Injection, USP (concentrate) should be stored between 20° to 25°C (68° to 77°F). [See USP Controlled Room Temperature]. DO NOT FREEZE. Store Upright.

Distributed by Hospira Inc., Lake Forest, IL 60045 USA

LAB-1310-2.0

Revised: 4/2021

MEDICATION GUIDE MitoXANTRONE (mito-xan-trone) Injection, USP (concentrate)

CONTAINS SODIUM METABISULFITE, A SULFITE THAT MAY CAUSE ALLERGIC-TYPE REACTIONS INCLUDING ANAPHYLACTIC SYMPTOMS AND LIFE-THREATENING OR LESS SEVERE ASTHMATIC EPISODES IN CERTAIN SUSCEPTIBLE PEOPLE. THE OVERALL PREVALENCE OF SULFITE SENSITIVITY IN THE GENERAL POPULATION IS UNKNOWN AND PROBABLY LOW. SULFITE SENSITIVITY IS SEEN MORE FREQUENTLY IN ASTHMATIC THAN IN NONASTHMATIC PEOPLE.

Read this Medication Guide before you start receiving MitoXANTRONE and each time you receive MitoXANTRONE. There may be new information. This information does not take the place of talking to your doctor about your medical condition or your treatment.

What is the most important information I should know about MitoXANTRONE?

MitoXANTRONE can cause serious side effects, including:

- decrease in the ability of your bone marrow to make blood cells (myelosuppression). Your doctor may do blood tests during treatment with MitoXANTRONE to check your blood cell counts. The symptoms of myelosuppression can include:
  - feeling tired
  - increased infections
  - bruising and bleeding easily
- heart problems (congestive heart failure) that may lead to death even in people who have never had heart problems before. Heart failure can happen while you receive MitoXANTRONE, or months to years after you stop receiving MitoXANTRONE. Your risk of heart failure increases the more MitoXANTRONE you receive.
  Call your doctor or get medical help right away if you have any of these problems during or after treatment with MitoXANTRONE:
  - shortness of breath
  - swelling of your ankles or feet
  - sudden weight gain
  - fast heartbeat or pounding in your chest
Before receiving MitoXANTRONE for the first time, you should have the following tests done:
  1. physical examination
  2. a test to check your heart's electrical activity (electrocardiogram)
  3. a test to check your heart's ability to pump blood
If you receive MitoXANTRONE to treat Multiple Sclerosis (MS), your doctor should also do the tests above:
  1. before you receive each MitoXANTRONE dose
  2. yearly after you stop receiving MitoXANTRONE treatment
- acute myeloid leukemia (AML). Receiving MitoXANTRONE increases your risk of AML. AML is a cancer of the blood-forming cells of your bone marrow. Symptoms of AML can include:

- feeling unusually tired and weak
- increased infections
- bruising and bleeding easily
- fever

- pain in your bones
- trouble breathing
- unexplained weight loss
- night sweats

- skin problems at your injection site. If MitoXANTRONE leaks out of your vein, skin problems can happen that may lead to serious skin damage (necrosis). Necrosis may need to be repaired surgically. Tell your doctor right away if you have any of the following problems at your injection site:

- redness
- swelling
- pain

- burning
- skin turns a bluish color

What is MitoXANTRONE?

MitoXANTRONE is a prescription medicine used alone or with other medicines to treat people with:

- secondary (chronic) progressive, progressive relapsing, or worsening relapsing-remitting multiple sclerosis (MS)
- pain related to advanced hormone-refractory prostate cancer
- acute nonlymphocytic leukemia (ANLL)

MitoXANTRONE is not for people with primary progressive MS. It is not known if MitoXANTRONE is safe and effective in children.

Who should not receive MitoXANTRONE?

Do not receive MitoXANTRONE if you are allergic to MitoXANTRONE or any of the ingredients in MitoXANTRONE. See the end of this Medication Guide for a complete list of ingredients in MitoXANTRONE.

What should I tell my doctor before receiving MitoXANTRONE?

Before you receive MitoXANTRONE, tell your doctor if you have:

- received MitoXANTRONE in the past
- heart problems
- liver problems
- kidney problems
- low blood cell counts
- an infection
- had radiation treatment in your chest area
- any other medical conditions
- are pregnant or plan to become pregnant. MitoXANTRONE may harm your unborn baby. Women who are able to become pregnant should use effective birth control (contraception) while using MitoXANTRONE and should have a pregnancy test, with known results, before receiving each dose of MitoXANTRONE. Talk to your doctor about using effective birth control while you receive MitoXANTRONE.
- are breastfeeding or plan to breastfeed. MitoXANTRONE can pass into your breast milk and may harm your baby. Talk to your doctor about the best way to feed your baby if you receive MitoXANTRONE. Do not breastfeed while receiving MitoXANTRONE.

Tell your doctor about all the medicines you take, including prescription and nonprescription medicines, vitamins, and herbal supplements.

Using MitoXANTRONE with certain other medicines may cause serious side effects.

Especially tell your doctor if you take or have taken:

- medicines for cancer treatment called anthracyclines or anthracenediones
- medicines that may affect your heart

Ask your doctor or pharmacist for a list of these medicines if you are not sure if you take or have taken any of these medicines.

Know the medicines you take. Keep a list of them to show your doctor and pharmacist when you get a new medicine.

How should I receive MitoXANTRONE?

- MitoXANTRONE is given by slow infusion through a needle placed in a vein (intravenous infusion) in your arm.
- Your doctor will tell you how often you will receive MitoXANTRONE.
- If you receive MitoXANTRONE to treat MS, your doctor should check how well your heart is working before each MitoXANTRONE dose. Talk to your doctor if you have not had your heart tests done before your MitoXANTRONE dose.
- Your doctor will do blood tests during your treatment with MitoXANTRONE to check your blood cell counts.
- If you are a woman of childbearing age taking MitoXANTRONE to treat MS, your doctor should do a pregnancy test before each MitoXANTRONE dose, even if you are using birth control.
- If you receive MitoXANTRONE to treat MS, there is a limit to the total amount of MitoXANTRONE you can receive during your lifetime. There is a higher risk of heart failure with increasing total lifetime doses of MitoXANTRONE.

What are the possible side effects of MitoXANTRONE?

MitoXANTRONE may cause serious side effects, including:

- See "What is the most important information I should know about MitoXANTRONE?" The most common side effects of MitoXANTRONE include:

- blue-green colored urine for about 24 hours after receiving MitoXANTRONE. This color change is harmless.
- bluish coloring of the whites of your eyes for about 24 hours after receiving MitoXANTRONE. This color change is harmless.

- nausea
- constipation
- diarrhea
- stomach pain
- hair loss

- fever and chills due to infections
- cough and sore throat due to upper respiratory tract infection
- mouth sores due to mouth infection
- loss of your menstrual period

Tell your doctor if you have any side effect that bothers you or that does not go away.

These are not all the possible side effects of MitoXANTRONE. For more information, ask your doctor or pharmacist.

Call your doctor for medical advice about side effects. You may report side effects to FDA at 1-800-FDA-1088.

General information about the safe and effective use of MitoXANTRONE.

Medicines are sometimes prescribed for purposes other than those listed in a Medication Guide.

This Medication Guide summarizes the most important information about MitoXANTRONE. If you would like more information, talk with your doctor. You can ask your pharmacist or doctor for information about MitoXANTRONE that is written for health professionals.

For more information go to www.pfizer.com or call 1-800-615-0187.

What are the ingredients in MitoXANTRONE?

Active ingredient: MitoXANTRONE hydrochloride

Inactive ingredients: sodium chloride, sodium metabisulfite, sodium acetate, and acetic acid

This Medication Guide has been approved by the U.S. Food and Drug Administration.

Distributed by Hospira Inc., Lake Forest, IL 60045 USA

LAB-1312-2.0

Revised: 7/2025

PRINCIPAL DISPLAY PANEL - 10 mL Vial Label

10 mL Vial
NDC 61703-343-18
Sterile

MitoXANTRONE Injection, USP
(concentrate)
20 mg/ 10 mL
(2 mg/mL)

Rx only

For IV Infusion After Dilution
Multiple-dose Vial Cytotoxic Agent
Pharmacist dispense enclosed medication guide to each patient.

Hospira

PRINCIPAL DISPLAY PANEL - 10 mL Vial Carton

VIAL

Hospira

1 x 10 mL Vial
NDC 61703-343-18

Sterile
Rx only

MitoXANTRONE
Injection, USP
(concentrate)
20 mg/ 10 mL
(2 mg/mL)

For Intravenous Infusion
After Dilution
Multiple-dose Vial

Pharmacist dispense enclosed
medication guide to each
patient.

Cytotoxic Agent

PRINCIPAL DISPLAY PANEL - 12.5 mL Vial Label

12.5 mL Vial
NDC 61703-343-65
Sterile

MitoXANTRONE
Injection, USP
(concentrate)
25 mg/ 12.5 mL
(2 mg/mL)

Rx only

For IV Infusion After Dilution
Multiple-dose Vial
Cytotoxic Agent

Pharmacist dispense enclosed
medication guide to each patient.

PRINCIPAL DISPLAY PANEL - 12.5 mL Vial Carton

VIAL

Hospira

1 x 12.5 mL Vial
NDC 61703-343-65

Sterile
Rx only

MitoXANTRONE
Injection, USP
(concentrate)

25 mg/ 12.5 mL
(2 mg/mL)

For Intravenous Infusion
After Dilution
Multiple-dose Vial

Pharmacist dispense
enclosed medication guide to
each patient.

Cytotoxic Agent

PRINCIPAL DISPLAY PANEL - 15 mL Vial Label

15 mL Vial
NDC 61703-343-66

Sterile
Rx only

MitoXANTRONE
Injection, USP
(concentrate)
30 mg/ 15 mL
(2 mg/mL)

For IV Infusion After Dilution
Multiple-dose Vial
Cytotoxic Agent

Pharmacist dispense enclosed
medication guide to each patient.

PRINCIPAL DISPLAY PANEL - 15 mL Vial Carton

VIAL

Hospira

1 x 15 mL Vial
NDC 61703-343-66

Sterile
Rx only

MitoXANTRONE
Injection, USP
(concentrate)

30 mg/ 15 mL
(2 mg/mL)

For Intravenous Infusion
After Dilution
Multiple-dose Vial

Pharmacist dispense
enclosed medication guide
to each patient.

Cytotoxic Agent